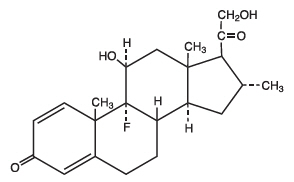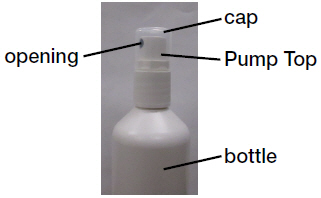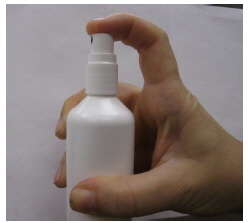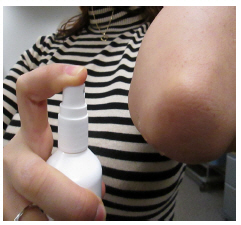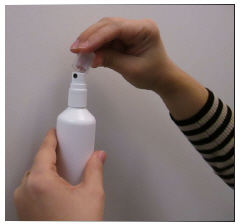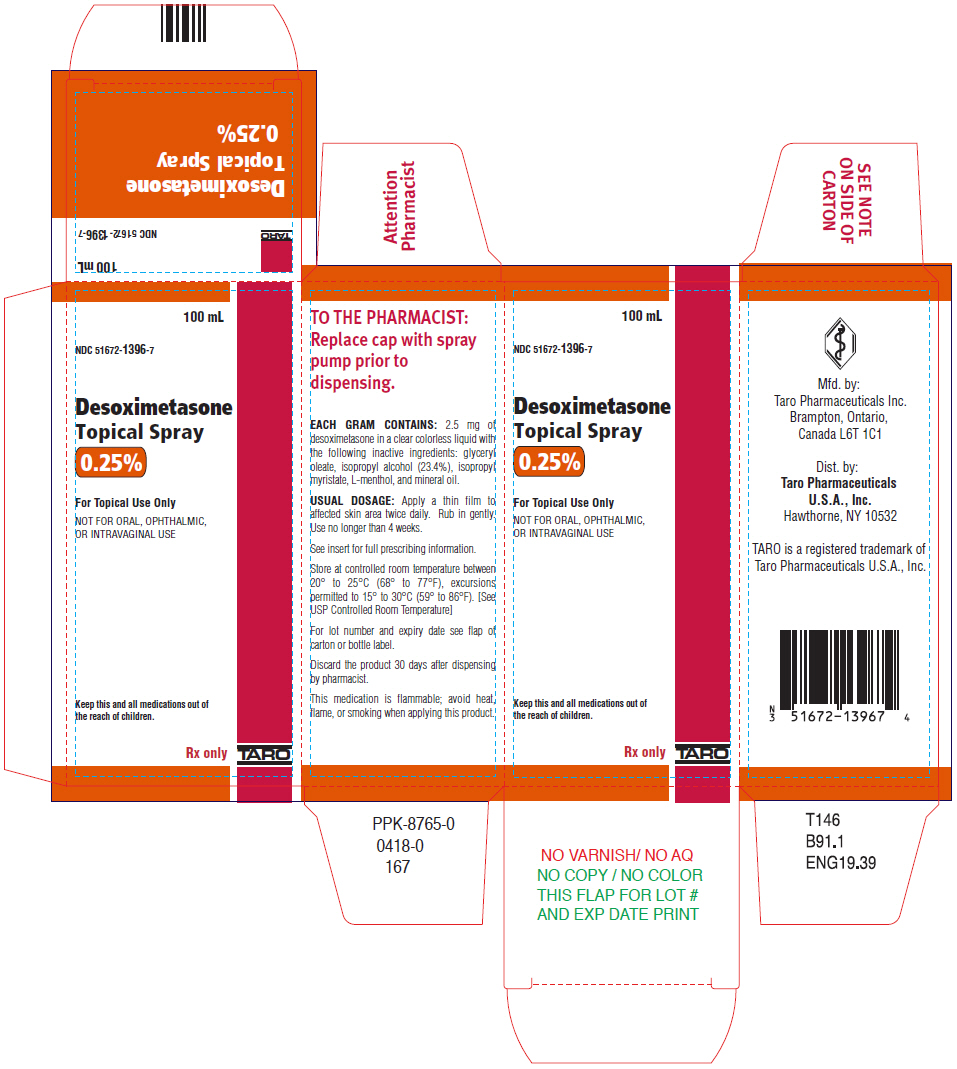 DRUG LABEL: Desoximetasone
NDC: 51672-1396 | Form: SPRAY
Manufacturer: Sun Pharmaceutical Industries, Inc.
Category: prescription | Type: HUMAN PRESCRIPTION DRUG LABEL
Date: 20250708

ACTIVE INGREDIENTS: DESOXIMETASONE 2.5 mg/1 mL
INACTIVE INGREDIENTS: GLYCERYL OLEATE; ISOPROPYL ALCOHOL; ISOPROPYL MYRISTATE; LEVOMENTHOL; MINERAL OIL

HIGHLIGHTS OF PRESCRIBING INFORMATION

These highlights do not include all the information needed to use Desoximetasone Topical Spray safely and effectively. See full prescribing information for Desoximetasone Topical Spray.
DESOXIMETASONE spray, for topical use
Initial U.S. Approval: 1977

1 INDICATIONS AND USAGE

Desoximetasone Topical Spray is a corticosteroid indicated for the treatment of plaque psoriasis in patients 18 years of age or older (1).

2 DOSAGE AND ADMINISTRATION

- Apply a thin film to the affected skin areas twice daily. Rub in gently. (2)
- Desoximetasone Topical Spray should be discontinued when control is achieved. (2)
- Treatment beyond 4 weeks is not recommended. (2)
- Do not use if atrophy is present at the treatment site. (2)
- Do not use with occlusive dressings, unless directed by the physician (2)
- Avoid use on the face, axilla or groin. (2)
- Desoximetasone Topical Spray is not for oral, ophthalmic, or intravaginal use. (2)

3 DOSAGE FORMS AND STRENGTHS

Spray, 0.25% w/w (3)

4 CONTRAINDICATIONS

None (4)

5 WARNINGS AND PRECAUTIONS

- Desoximetasone Topical Spray can produce reversible HPA axis suppression with the potential for glucocorticosteroid insufficiency during or after treatment. (5.1)
- Cushing's syndrome, hyperglycemia, and unmasking of latent diabetes mellitus can result from systemic absorption of topical corticosteroids. (5.1)
- Because of the potential for systemic absorption, use of topical corticosteroids may require that patients be periodically evaluated for HPA axis suppression. (5.1)
- Modify use if HPA axis suppression develops. (5.1)
- High potency corticosteroids, large treatment surface areas, prolonged use, use of occlusive dressings, altered skin barrier, liver failure and young age may predispose patients to HPA axis suppression. (5.1)
- Pediatric patients may be more susceptible to systemic toxicity when treated with topical corticosteroids. (5.1, 8.4)
- Desoximetasone Topical Spray is flammable; keep away from heat or flame. (5.5)

6 ADVERSE REACTIONS

The most common adverse reactions (≥ 1%) are application site dryness, application site irritation and application site pruritus. (6.1)

To report SUSPECTED ADVERSE REACTIONS, contact Taro Pharmaceuticals, U.S.A., Inc., at 1-866-923-4914 or FDA at 1-800-FDA-1088 or www.fda.gov/medwatch.

FULL PRESCRIBING INFORMATION

1 INDICATIONS AND USAGE

Desoximetasone Topical Spray is a corticosteroid indicated for the treatment of plaque psoriasis in patients 18 years of age or older.

2 DOSAGE AND ADMINISTRATION

Apply Desoximetasone Topical Spray as a thin film to the affected skin areas twice daily. Rub in gently.

The treated skin area should not be bandaged or otherwise covered or wrapped unless directed by the physician.

Desoximetasone Topical Spray should be discontinued when control is achieved.

Treatment beyond 4 weeks is not recommended.

Do not use if atrophy is present at the treatment site.

Avoid use on the face, axilla or groin.

Desoximetasone Topical Spray is for external use only. It is not for oral, ophthalmic, or intravaginal use.

3 DOSAGE FORMS AND STRENGTHS

Topical Spray, 0.25%. Each gram of Desoximetasone Topical Spray contains 2.5 mg of desoximetasone in a clear, colorless liquid.

4 CONTRAINDICATIONS

None

5 WARNINGS AND PRECAUTIONS

5.1 Effect on Endocrine System

Desoximetasone Topical Spray is a topical corticosteroid that has been shown to suppress the hypothalamic-pituitary-adrenal (HPA) axis.

Systemic absorption of topical corticosteroids can produce reversible HPA axis suppression with the potential for glucocorticosteroid insufficiency. This may occur during treatment or upon withdrawal of the topical corticosteroid.

In a study including 21 evaluable subjects 18 years of age or older with moderate to severe plaque psoriasis, adrenal suppression was identified in 1 out of 12 subjects having involvement of 10 to 15% of body surface area (BSA) and 2 out of 9 subjects having involvement of >15% of BSA after treatment with Desoximetasone Topical Spray twice a day for 28 days. [ see Clinical Pharmacology (12.2)]

Because of the potential for systemic absorption, use of topical corticosteroids may require that patients be periodically evaluated for HPA axis suppression. Factors that predispose a patient using a topical corticosteroid to HPA axis suppression include the use of high potency steroids, larger treatment surface areas, prolonged use, use of occlusive dressings, altered skin barrier, liver failure and young age.

An ACTH stimulation test may be helpful in evaluating patients for HPA axis suppression.

If HPA axis suppression is documented, an attempt should be made to gradually withdraw the drug, to reduce the frequency of application, or to substitute a less potent steroid. Manifestations of adrenal insufficiency may require supplemental systemic corticosteroids. Recovery of HPA axis function is generally prompt and complete upon discontinuation of topical corticosteroids.

Cushing's syndrome, hyperglycemia, and unmasking of latent diabetes mellitus can also result from systemic absorption of topical corticosteroids.

Use of more than one corticosteroid-containing product at the same time may increase the total systemic corticosteroid exposure.

Pediatric patients may be more susceptible to systemic toxicity from use of topical corticosteroids. [ see Use in Specific Populations (8.4)]

5.2 Local Adverse Reactions with Topical Corticosteroids

Local adverse reactions may be more likely to occur with occlusive use, prolonged use or use of higher potency corticosteroids. Reactions may include atrophy, striae, telangiectasias, burning, itching, irritation, dryness, folliculitis, acneiform eruptions, hypopigmentation, perioral dermatitis, allergic contact dermatitis, secondary infection, and miliaria. Some local adverse reactions may be irreversible.

5.3 Allergic Contact Dermatitis with Topical Corticosteroids

Allergic contact dermatitis to any component of topical corticosteroids is usually diagnosed by a failure to heal rather than a clinical exacerbation. Clinical diagnosis of allergic contact dermatitis can be confirmed by patch testing.

5.4 Concomitant Skin Infections

Concomitant skin infections should be treated with an appropriate antimicrobial agent.

If the infection persists, Desoximetasone Topical Spray should be discontinued until the infection has been adequately treated.

5.5 Flammable Contents

Desoximetasone Topical Spray is flammable; keep away from heat or flame.

6 ADVERSE REACTIONS

6.1 Clinical Trials Experience

Because clinical trials are conducted under widely varying conditions, adverse reaction rates observed in the clinical trials of a drug cannot be directly compared to rates in the clinical trials of another drug and may not reflect the rates observed in practice.

In randomized, multicenter, prospective vehicle-controlled clinical trials, subjects with moderate to severe plaque psoriasis of the body applied Desoximetasone Topical Spray or vehicle spray twice daily for 4 weeks. A total of 149 subjects applied Desoximetasone Topical Spray.

Adverse reactions that occurred in ≥ 1% of subjects treated with Desoximetasone Topical Spray were application site dryness (2.7%), application site irritation (2.7%) and application site pruritus (2.0%).

Another less common adverse reaction (<1% but >0.1%) was folliculitis.

Table 1. Number (%) of Subjects with Adverse Reactions Occurring in ≥ 1%
 | Desoximetasone Topical Spray, 0.25% b.i.d. (N = 149) | Vehicle spray b.i.d. (N = 135)
Number of Subjects with Adverse Reactions | 13 (8.7%) | 18 (13.3%)
Application site dryness | 4 (2.7%) | 7 (5.2%)
Application site irritation | 4 (2.7%) | 5 (3.7%)
Application site pruritus | 3 (2.0%) | 5 (3.7%)

8 USE IN SPECIFIC POPULATIONS

8.1 Pregnancy

Teratogenic Effects: Pregnancy Category C

There are no adequate and well-controlled studies in pregnant women. Desoximetasone Topical Spray should be used during pregnancy only if the potential benefit justifies the potential risk to the fetus.

Corticosteroids have been shown to be teratogenic in laboratory animals when administered systemically at relatively low dosage levels.

Desoximetasone has been shown to be teratogenic and embryotoxic in mice, rats, and rabbits when given by subcutaneous or dermal routes of administration at doses 3 to 30 times the human dose of Desoximetasone Topical Spray based on a body surface area comparison.

8.3 Nursing Mothers

Systemically administered corticosteroids appear in human milk and could suppress growth, interfere with endogenous corticosteroid production, or cause other untoward effects. It is not known whether topical administration of corticosteroids could result in sufficient systemic absorption to produce detectable quantities in breast milk. Because many drugs are excreted in human milk, caution should be exercised when Desoximetasone Topical Spray is administered to a nursing woman.

If used during lactation, Desoximetasone Topical Spray should not be applied on the chest to avoid accidental ingestion by the infant.

8.4 Pediatric Use

Safety and effectiveness of Desoximetasone Topical Spray in patients younger than 18 years of age have not been studied; therefore use in pediatric patients is not recommended. Because of a higher ratio of skin surface area to body mass, pediatric patients are at a greater risk than adults of HPA axis suppression and Cushing's syndrome when they are treated with topical corticosteroids. They are therefore at greater risk of adrenal insufficiency during and/or after withdrawal of treatment. Adverse effects including striae have been reported with inappropriate use of topical corticosteroids in infants and children. [ see Warnings and Precautions (5.1)]

HPA axis suppression, Cushing's syndrome, linear growth retardation, delayed weight gain, and intracranial hypertension have been reported in children receiving topical corticosteroids. Manifestations of adrenal suppression in children include low plasma cortisol levels and absence of response to ACTH stimulation. Manifestations of intracranial hypertension include bulging fontanelles, headaches, and bilateral papilledema. [ see Warnings and Precautions (5.1)]

8.5 Geriatric Use

Clinical studies of Desoximetasone Topical Spray did not include sufficient numbers of subjects aged 65 years and over to determine whether they respond differently from younger subjects. Other reported clinical experience has not identified differences in responses between the elderly and younger patients. In general, dose selection for an elderly patient should be cautious, usually starting at the low end of the dosing range, reflecting the greater frequency of decreased hepatic, renal, or cardiac function, and of concomitant disease or other drug therapy.

10 OVERDOSAGE

Desoximetasone Topical Spray can be absorbed in sufficient amounts to produce systemic effects. [ see Warnings and Precautions (5.1)]

11 DESCRIPTION

Desoximetasone Topical Spray, 0.25% contains desoximetasone as the active ingredient.

Desoximetasone is a corticosteroid with the chemical name of pregna-1, 4-diene-3, 20-dione, 9-fluoro-11, 21-dihydroxy-16-methyl-, (11β,16α)-.

Desoximetasone has the molecular formula of C22H29FO4and a molecular weight of 376.47. The CAS Registry Number is 382-67-2.

The structural formula is:

Each gram of Desoximetasone Topical Spray contains 2.5 mg of desoximetasone in a clear, colorless liquid with the following inactive ingredients: glyceryl oleate, isopropyl alcohol (23.4%), isopropyl myristate, L-menthol, and mineral oil. Desoximetasone Topical Spray is co-packaged with a manual spray pump for installation by the pharmacist prior to dispensing to patients.

12 CLINICAL PHARMACOLOGY

12.1 Mechanism of Action

Corticosteroids play a role in cellular signaling, immune function, inflammation and protein regulation; however, the precise mechanism of action in psoriasis is unknown.

12.2 Pharmacodynamics

Vasoconstrictor studies performed with Desoximetasone Topical Spray in healthy subjects indicate that it is in the high to super-high range of potency as compared with other topical corticosteroids.

The potential for hypothalamic-pituitary-adrenal (HPA) axis suppression was evaluated in a study of 24 adult subjects with moderate to severe plaque psoriasis. Desoximetasone Topical Spray was applied twice a day for 28 days. Twenty-one subjects had evaluable serum cortisol levels. The proportion of subjects demonstrating HPA axis suppression was 8.3% (1 out of 12) in subjects having psoriasis involvement of 10 to 15% of body surface area (BSA), and 22.2% (2 out of 9) in subjects having psoriasis involvement of > 15% of their BSA. In this study HPA axis suppression was defined as serum cortisol level ≤18 mcg/dL 30-min post cosyntropin stimulation. In the 2 subjects with available follow-up values, suppression reversed 28 days after the end of treatment.

12.3 Pharmacokinetics

The extent of percutaneous absorption of topical corticosteroids is determined by many factors including the vehicle, the integrity of the epidermal barrier, and the use of occlusive dressings.

Topical corticosteroids can be absorbed from normal intact skin. Inflammation and/or other disease processes in the skin increase percutaneous absorption. Occlusive dressings substantially increase the percutaneous absorption of topical corticosteroids. Once absorbed through the skin, topical corticosteroids are handled through pharmacokinetic pathways similar to systemically administered corticosteroids. Corticosteroids are bound to plasma proteins in varying degrees. Corticosteroids are metabolized primarily in the liver and are then excreted by the kidneys. Some of the topical corticosteroids and their metabolites are also excreted into the bile.

Plasma concentrations of desoximetasone were measured at two single random time points in the HPA axis suppression trial in 24 subjects with psoriasis [ see Clinical Pharmacology (12.2)]. The mean (% Coefficient of Variation) concentration of desoximetasone was 449 pg/mL (86%) at Day 14 and 678 pg/mL (135%) at Day 28. The concentration time profile following application of Desoximetasone Topical Spray is not known.

13 NONCLINICAL TOXICOLOGY

13.1 Carcinogenesis, Mutagenesis, Impairment of Fertility

Long-term animal studies have not been performed to evaluate the carcinogenic potential of Desoximetasone Topical Spray.

In a 13-week repeat-dose toxicity study in rats, topical administration of desoximetasone spray at concentrations of 0.001, 0.005 and 0.02% BID (which corresponds to dose levels of 0.01, 0.05, or 0.2 mg/kg/dose BID, respectively) resulted in a toxicity profile consistent with long-term exposure to corticosteroids, including adrenal atrophy and histopathological changes in several organ systems indicative of severe immune suppression. A no observable adverse effect level (NOAEL) could not be determined in this study. Although the clinical relevance of the findings in animals to humans is not clear, sustained glucocorticoid-related immune suppression may increase the risk of infection and possibly the risk for carcinogenesis.

Desoximetasone revealed no evidence of mutagenic or clastogenic potential based on the results of two in vitrogenotoxicity tests (Ames assay and Chinese hamster ovary cell chromosome aberration assay) and one in vivogenotoxicity test (mouse bone marrow micronucleus assay).

No evidence of impairment of male or female fertility was observed at subcutaneous desoximetasone doses up to 0.1 mg/kg/day (0.6 mg/m^2/day) in Sprague-Dawley rats.

14 CLINICAL STUDIES

Two multi-center, randomized, double-blind, vehicle-controlled clinical trials were conducted in 239 subjects aged 18 years and older with moderate to severe plaque psoriasis of the body. In both trials, randomized subjects applied Desoximetasone Topical Spray or vehicle spray to the affected areas twice daily for 4 weeks. Enrolled subjects had a minimum body surface area of involvement of 10%, and a Physician's Global Assessment score (PGA) of 3 (moderate) or 4 (severe).

Efficacy was assessed at Week 4 as the proportion of subjects who were considered a Clinical Success ("clear" (0) or "almost clear" (1) according to the PGA scale). Table 2 presents the efficacy results.

Table 2. Number of Subjects (%) with Clinical Success (scored as clear or almost clear) at Week 4.
Parameter | Trial 1 |  | Trial 2
 | Desoximetasone | Vehicle | Desoximetasone | Vehicle
 | N=59 | N=60 | N=60 | N=60
Clinical Success | 18 (30.5%) | 3 (5.0%) | 32 (53.3%) | 11 (18.3%)

16 HOW SUPPLIED/STORAGE AND HANDLING

16.1 How Supplied/Storage

Desoximetasone Topical Spray, 0.25% is a clear colorless liquid supplied in white, opaque bottles with white, opaque screw caps in the following sizes:

- 30 mL
- 50 mL
- 100 mL (2-50 mL bottles)
- 100 mL

- (NDC 51672-1396-3)
- (NDC 51672-1396-4)
- (NDC 51672-1396-6)
- (NDC 51672-1396-7)

STORAGE AND HANDLING

Store at controlled room temperature between 20°C to 25°C (68°F to 77°F), excursions permitted to 15°C to 30°C (59°F to 86°F). [See USP Controlled Room Temperature]

Spray is flammable; avoid heat, flame or smoking when using this product.

Each unit is co-packaged with a manual spray pump for installation by the pharmacist.

16.2 Instructions for the Pharmacist

1. Remove the spray pump from the wrapper
2. Remove and discard the cap from the bottle
3. Keeping the bottle vertical, insert the spray pump into the bottle and turn clockwise until well-fastened
4. Dispense the bottle with the spray pump inserted
5. Label the bottle with "discard the product 30 days after dispensing"

17 PATIENT COUNSELING INFORMATION

See FDA-approved patient labeling (Patient Informationand Instructions for Use)

Inform patients of the following:

- Use this medication as directed by the physician.
- Desoximetasone Topical Spray is for external use only. Avoid use on the face, axilla or groin.
- Do not to use this medication for any disorder other than that for which it was prescribed.
- Do not bandage or otherwise cover or wrap the treated skin so as to be occlusive.
- Report any signs of local or systemic adverse reactions to the physician.
- Do not use other corticosteroid-containing products with Desoximetasone Topical Spray without first consulting with the physician.
- Discontinue therapy when control is achieved. If no improvement is seen within 4 weeks, contact the physician.
- This medication is flammable; avoid heat, flame, or smoking when applying this product.
- Discard this product 30 days after dispensed by pharmacist.

Mfd. by: Taro Pharmaceuticals Inc., Brampton, Ontario, Canada L6T 1C1

Dist. by: Taro Pharmaceuticals U.S.A., Inc., Hawthorne, NY 10532

Revised: December 2019
PPK-8767-1
110

Instructions for Use Desoximetasone (des ox'' i met' a sone) Topical Spray

Important information: Desoximetasone Topical Spray is for use on skin only.Do not get Desoximetasone Topical Spray near or in your mouth, eyes or vagina.

Read the Instructions for Use that comes with Desoximetasone Topical Spray before you start using it and each time you get a refill. There may be new information. This information does not take the place of talking with your doctor about your medical condition or your treatment.

Parts of Desoximetasone Topical Spray bottle (See Figure A)

Figure A

How to apply Desoximetasone Topical Spray: Step 1:Remove the cap from the pump top.

Step 2:Hold the bottle in an upright position while pointing the opening of the pump top in the direction of the affected area. To spray, push down on the pump top. Apply Desoximetasone Topical Spray to the affected area as instructed by your doctor. (See Figure B) | Figure B | Step 3:Spray only enough Desoximetasone Topical Spray to cover the affected area, for example, the elbow (See Figure C). Rub in Desoximetasone Topical Spray gently. | Figure C

Repeat Steps 2 and 3 to apply Desoximetasone Topical Spray to other affected areas as instructed by your doctor.

Step 4:After applying Desoximetasone Topical Spray, place the cap back onto the pump top. (See Figure D)

This Patient Information and Instructions for Use have been approved by the U.S. Food and Drug Administration.

Mfd. by: Taro Pharmaceuticals Inc., Brampton, Ontario, Canada L6T 1C1

Dist. by: Taro Pharmaceuticals U.S.A., Inc., Hawthorne, NY 10532

Issued: April, 2018
PPK-8768-0
167

PATIENT INFORMATION
Desoximetasone (des ox'' i met' a sone)
Topical Spray

Important information: Desoximetasone Topical Spray is for use on skin only.Do not get Desoximetasone Topical Spray near or in your eyes, mouth or vagina.

What is Desoximetasone Topical Spray?

- Desoximetasone Topical Spray is a prescription corticosteroid medicine used to treat plaque psoriasis of the body in people 18 years of age and older.
- You should not use Desoximetasone Topical Spray on your face, underarms (armpits), or groin areas.
- It is not known if Desoximetasone Topical Spray is safe and effective in children under 18 years of age. Desoximetasone Topical Spray should not be used in children under 18 years of age.

Before you use Desoximetasone Topical Spray, tell your doctor if you:

- are allergic to any of the ingredients in Desoximetasone Topical Spray. See the end of this leaflet for a list of the ingredients in Desoximetasone Topical Spray.
- have a skin infection. You may need medicine to treat the skin infection before you use Desoximetasone Topical Spray.
- have thinning of the skin (atrophy) at the treatment site
- have any other medical conditions
- are pregnant or plan to become pregnant. It is not known if Desoximetasone Topical Spray will harm your unborn baby.
- are breastfeeding or plan to breastfeed. It is not known if Desoximetasone Topical Spray passes into your breast milk. Do not apply Desoximetasone Topical Spray to your chest area if you are breastfeeding. This will help to prevent your baby from accidentally getting Desoximetasone Topical Spray into the mouth.

Tell your doctor about all the medicines you takeincluding prescription and over-the-counter medicines, vitamins and herbal supplements. Especially tell your doctor if you take other corticosteroid medicines by mouth or use other products on your skin that contain corticosteroids.

What should I avoid while using Desoximetasone Topical Spray?

Desoximetasone Topical Spray is flammable.Avoid heat, flames or smoking while applying Desoximetasone Topical Spray to your skin.

How should I use Desoximetasone Topical Spray?

- Use Desoximetasone Topical Spray exactly as your doctor tells you to use it.
- Apply Desoximetasone Topical Spray 2 times a day.
- Do not bandage, cover, or wrap the treated skin area.
- Desoximetasone Topical Spray should be used for the shortest amount of time needed to treat your plaque psoriasis. Tell your doctor if your skin condition is not getting better after 4 weeks of using Desoximetasone Topical Spray. You should not use Desoximetasone Topical Spray for longer than 4 weeks.
- Wash your hands after applying Desoximetasone Topical Spray.
- Safely throw away (discard) any unused Desoximetasone Topical Spray after 30 days.

See the " Instructions for Use" at the end of the Patient Information for detailed information about the right way to apply Desoximetasone Topical Spray.

What are the possible side effects of Desoximetasone Topical Spray?

Desoximetasone Topical Spray may cause serious side effects, including:

- Desoximetasone Topical Spray can pass through your skin.Too much Desoximetasone Topical Spray passing through your skin can cause your adrenal glands to stop working. Your doctor may do blood tests to check for adrenal gland problems.

The most common side effects of Desoximetasone Topical Spray includedryness, irritation and itching of skin at the treated site.

Tell your doctor if you have any side effect that bothers you or that does not go away. These are not all the possible side effects of Desoximetasone Topical Spray. For more information, ask your doctor.

Call your doctor for medical advice about side effects. You may report side effects to FDA at 1-800-FDA-1088. For more information go to dailymed.nlm.nih.gov.

How should I store Desoximetasone Topical Spray?

- Store Desoximetasone Topical Spray at room temperature between 68˚F to 77˚F (20˚C to 25˚C).
- Keep Desoximetasone Topical Spray and all medicines out of the reach of children.

General information about the safe and effective use of Desoximetasone Topical Spray.

- Do not use Desoximetasone Topical Spray for a condition for which it was not prescribed. If you would like more information, talk with your doctor. You can ask your pharmacist or doctor for information about Desoximetasone Topical Spray that is written for health professionals.

What are the ingredients in Desoximetasone Topical Spray?

Active ingredient:desoximetasone

Inactive ingredients:glyceryl oleate, isopropyl alcohol, isopropyl myristate, L-menthol, and mineral oil

Mfd. by: Taro Pharmaceuticals Inc., Brampton, Ontario, Canada L6T 1C1

Dist. by: Taro Pharmaceuticals U.S.A., Inc., Hawthorne, NY 10532

Issued: April, 2018
PPK-8768-0
167

PRINCIPAL DISPLAY PANEL - 100 mL Bottle Carton

100 mL

NDC 51672-1396-7

Desoximetasone
Topical Spray

0.25%

For Topical Use Only

NOT FOR ORAL, OPHTHALMIC,
OR INTRAVAGINAL USE

Keep this and all medications out of
the reach of children.

Rx only

TARO